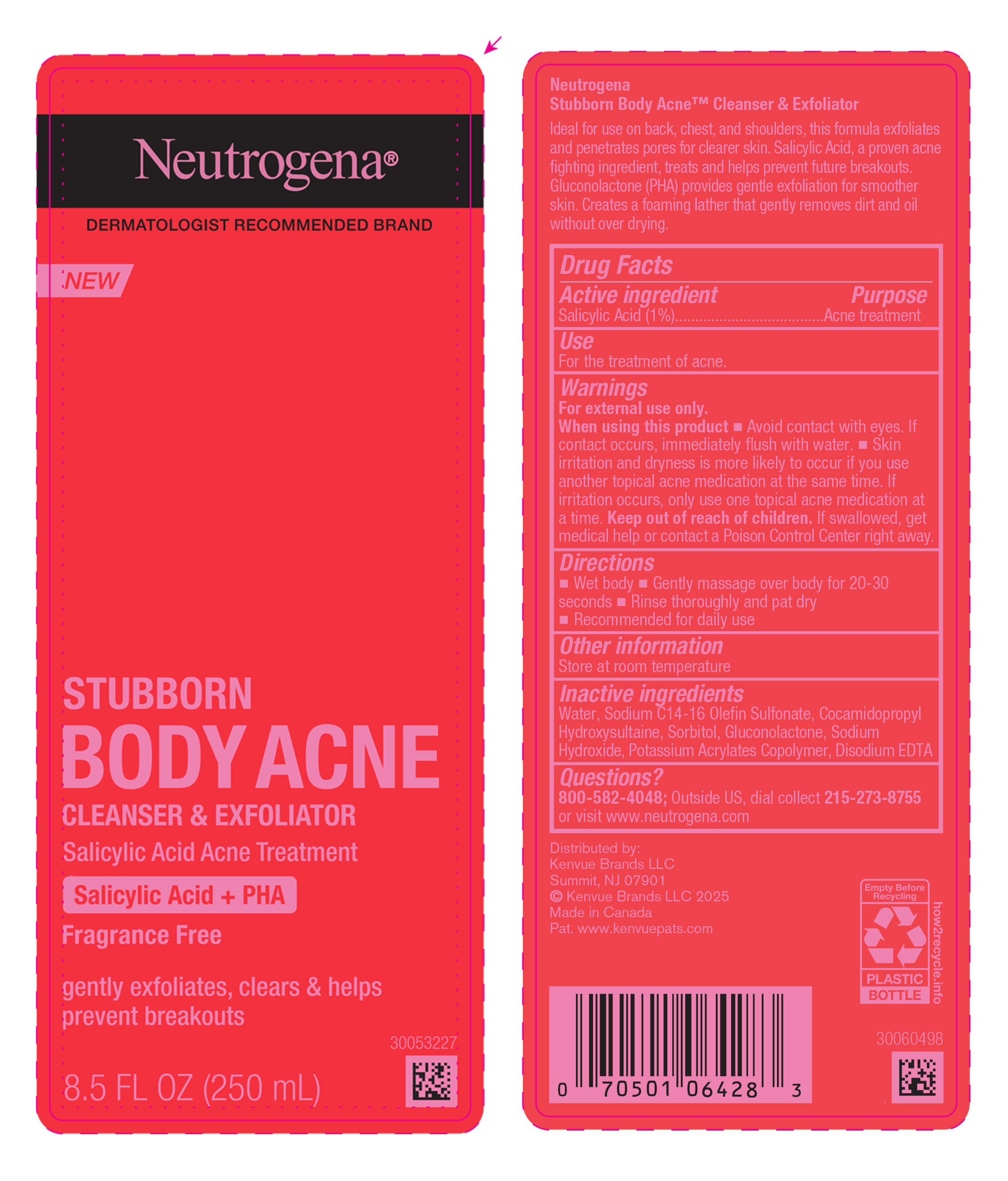 DRUG LABEL: Neutrogena Stubborn Body Acne Cleanser and Exfoliator
NDC: 69968-0759 | Form: LIQUID
Manufacturer: Kenvue Brands LLC
Category: otc | Type: HUMAN OTC DRUG LABEL
Date: 20250526

ACTIVE INGREDIENTS: SALICYLIC ACID 10 mg/1 mL
INACTIVE INGREDIENTS: GLUCONOLACTONE; EDETATE DISODIUM ANHYDROUS; SODIUM C14-16 OLEFIN SULFONATE; COCAMIDOPROPYL HYDROXYSULTAINE; WATER; SORBITOL; SODIUM HYDROXIDE

Neutrogena Stubborn Body Acne Cleanser and Exfoliator

Drug Facts

Active ingredient

Salicylic Acid (1%)

Purpose

Acne treatment

Use

For the treatment of acne.

Warnings

For external use only.

When using this product

- ▪ Avoid contact with eyes. If contact occurs, immediately flush with water.
  ▪ Skin irritation and dryness is more likely to occur if you use another topical acne medication at the same time. If irritation occurs, only use one topical acne medication at a time.

Keep out of reach of children. If swallowed, get medical help or contact a Poison Control Center right away.

Directions

▪ Wet body

▪ Gently massage over body for 20-30 seconds

▪ Rinse thoroughly and pat dry

▪ Recommended for daily use

Other Information

- Store at room temperature

Inactive ingredients

Water, Sodium C14-16 Olefin Sulfonate, Cocamidopropyl Hydroxysultaine, Sorbitol, Gluconolactone, Sodium Hydroxide, Potassium Acrylates Copolymer, Disodium EDTA

Questions?

800-582-4048; Outside US, dial collect 215-273-8755 or visit www.neutrogena.com

Distributed by:

Kenvue Brands LLC

Summit, NJ 07901

PRINCIPAL DISPLAY PANEL - 250mL Bottle

Neutrogena®

DERMATOLOGIST RECOMMENDED BRAND

NEW

STUBBORN

BODY ACNE

CLEANSER & EXFOLIATOR

Salicylic Acid Acne Treatment

Salicylic Acid + PHA

Fragrance Free

gently exfoliates, clears & helps

prevent breakouts

8.5 FL OZ (250mL)